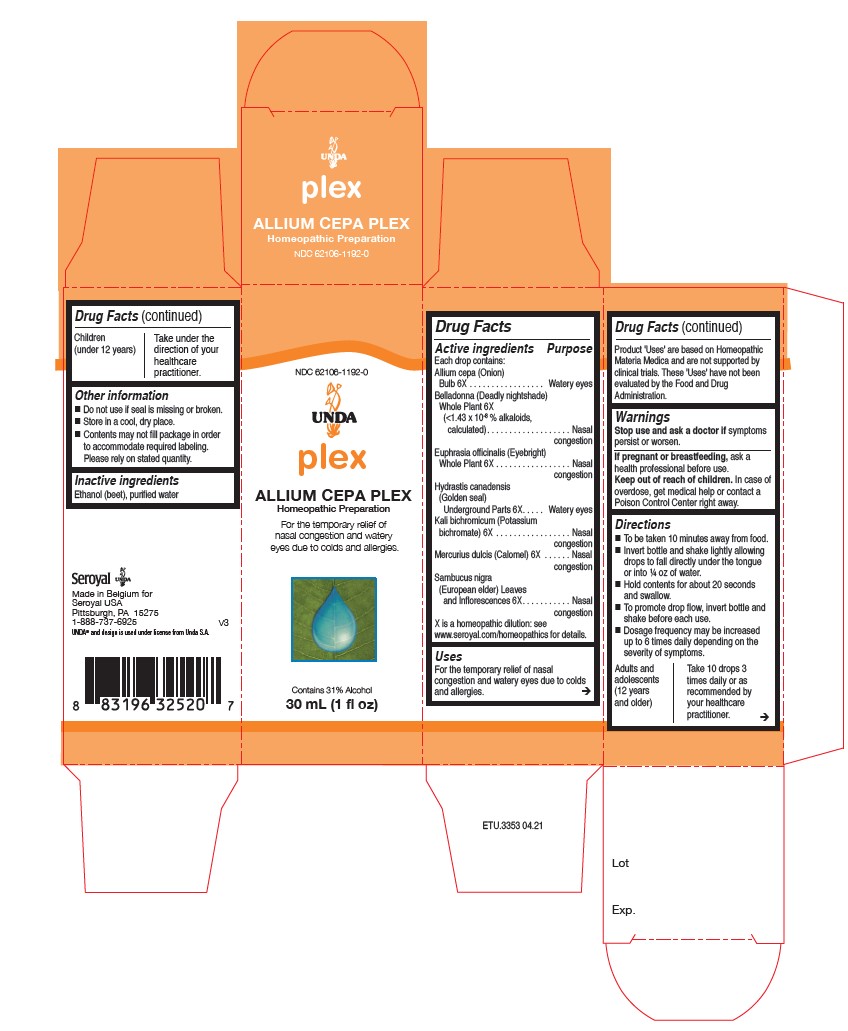 DRUG LABEL: ALLIUM CEPA PLEX
NDC: 62106-1192 | Form: LIQUID
Manufacturer: Seroyal USA
Category: homeopathic | Type: HUMAN OTC DRUG LABEL
Date: 20210714

ACTIVE INGREDIENTS: EUPHRASIA STRICTA 6 [hp_X]/30 mL; ONION 6 [hp_X]/30 mL; ATROPA BELLADONNA WHOLE 6 [hp_X]/30 mL; GOLDENSEAL 6 [hp_X]/30 mL; POTASSIUM DICHROMATE 6 [hp_X]/30 mL; CALOMEL 6 [hp_X]/30 mL; SAMBUCUS NIGRA FLOWERING TOP 6 [hp_X]/30 mL
INACTIVE INGREDIENTS: WATER; ALCOHOL

ALLIUM CEPA PLEX

Active ingredients

Each drop contains:

Allium cepa (Onion) Bulb 6X
Belladonna (Deadly nightshade) Whole Plant 6X (<1.43 x 10-8 % alkaloids, calculated)
Euphrasia officinalis (Eyebright) Whole Plant 6X
Hydrastis canadensis (Golden seal) Underground Parts 6X
Kali bichromicum (Potassium bichromate) 6X
Mercurius dulcis (Calomel) 6X
Sambucus nigra (European elder) Leaves and Inflorescences 6X

Uses

For the temporary relief of nasal congestion and watery eyes due to colds and allergies.

Warnings
Stop use and ask a doctor if symptoms persist or worsen.
If pregnant or breastfeeding, ask a health professional before use.
Keep out of reach of children.

In case of overdose, get medical help or contact a Poison Control Center right away.

Stop use and ask a doctor if symptoms persist or worsen.

PREGNANCY OR BREAST FEEDING

If pregnant or breastfeeding, ask a health professional before use.

Keep out of reach of children.

OVERDOSAGE

In case of overdose, get medical help or contact a Poison Control Center right away.

Inactive ingredients
Ethanol (beet), purified water

Other information
Do not use if seal is missing or broken.
Store in a cool, dry place.

Contents may not fill package in order to accommodate required labeling. Please rely on stated quantity.

Directions

To be taken ten minutes away from food.
Invert bottle and shake lightly allowing drops to fall directly under the tongue or into ¼ oz of water.
Hold contents for about 20 seconds and swallow.
To promote drop flow, invert bottle and shake before each use.
Dosage frequency may be increased up to six times daily depending on the severity of symptoms.

Adults and adolescents (12 years and older)

Take 10 drops three times daily or as recommended by your healthcare practitioner.

Children (under 12 years)

Take under the direction of your healthcare practitioner.

Uses

For the temporary relief of nasal congestion and watery eyes due to colds and allergies.

Directions

To be taken ten minutes away from food.
Invert bottle and shake lightly allowing drops to fall directly under the tongue or into ¼ oz of water.
Hold contents for about 20 seconds and swallow.
To promote drop flow, invert bottle and shake before each use.
Dosage frequency may be increased up to six times daily depending on the severity of symptoms.

Adults and adolescents (12 years and older)

Take 10 drops three times daily or as recommended by your healthcare practitioner.

Children (under 12 years)

Take under the direction of your healthcare practitioner.

PACKAGE LABEL

NDC 62106-1192-0

UNDA

plex

ALLIUM CEPA PLEX

Homeopathic Preparation

For the temporary relief of nasal congestion

and watery eyes due to colds and allergies.

Contains 30% Alcohol
1 fl oz (30 mL)